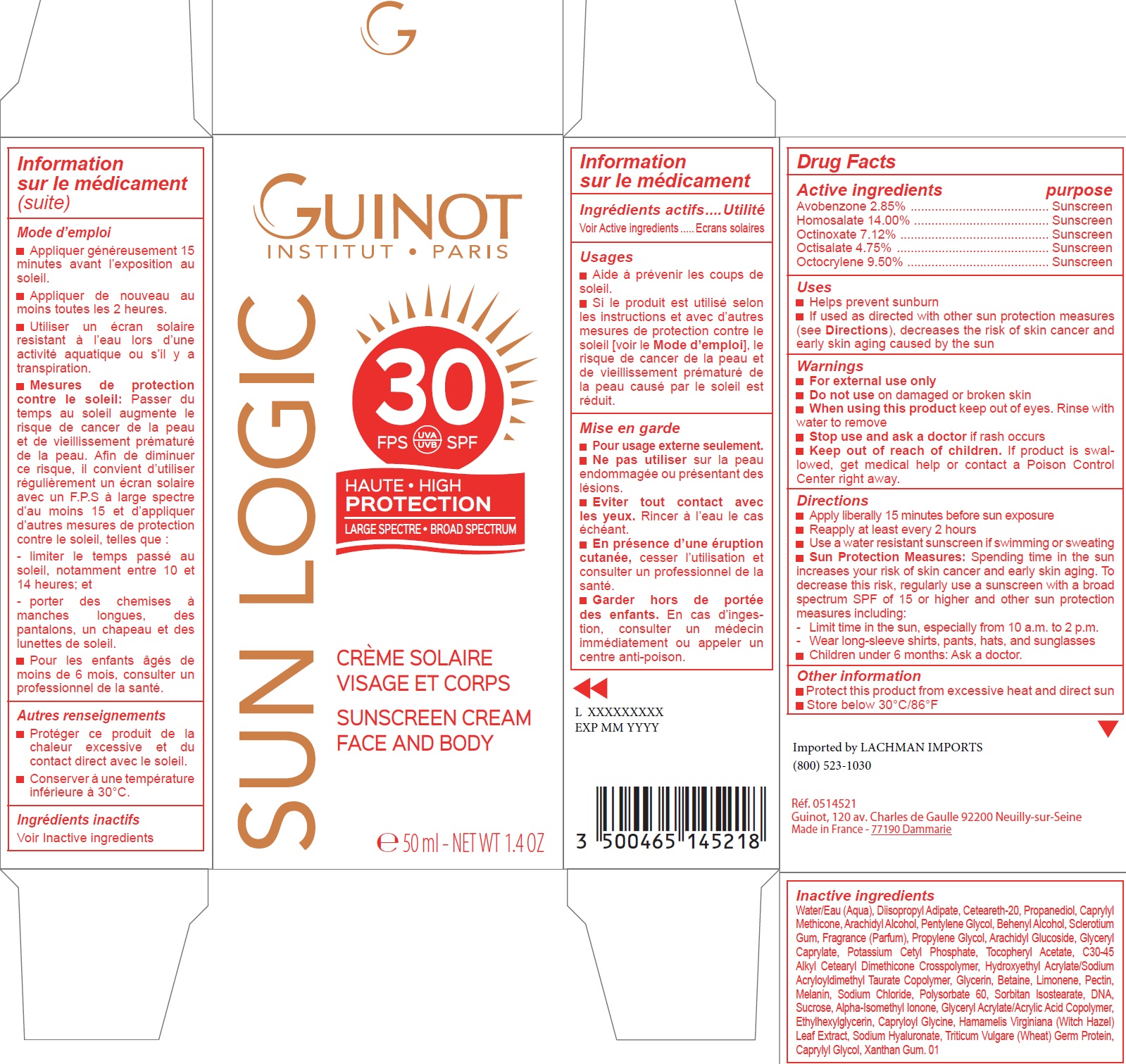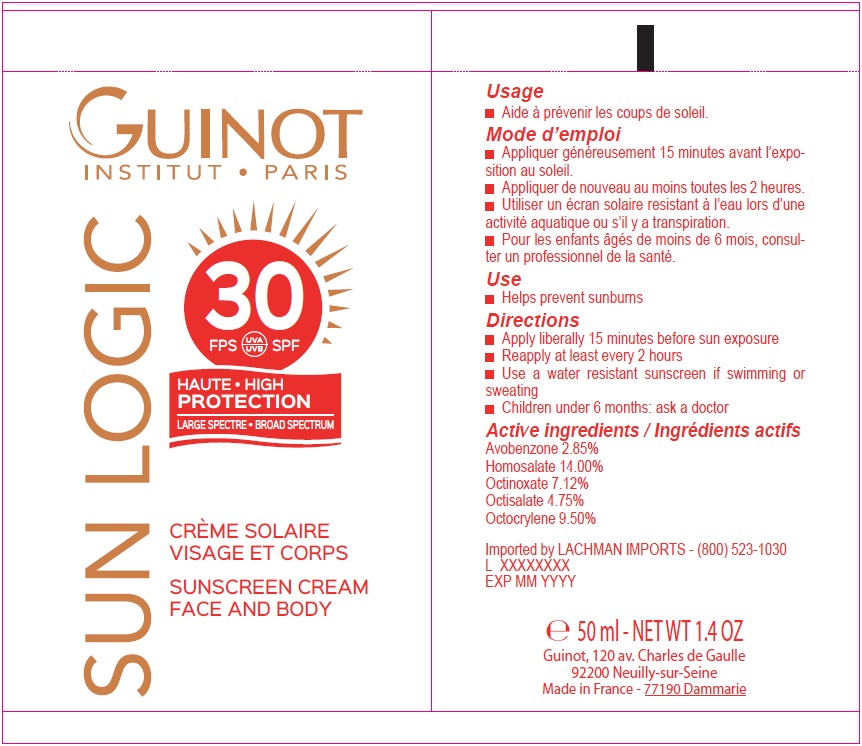 DRUG LABEL: Sun Logic Creme Solaire Visage et corps SPF 30
NDC: 54181-011 | Form: LOTION
Manufacturer: Guinot
Category: otc | Type: HUMAN OTC DRUG LABEL
Date: 20251229

ACTIVE INGREDIENTS: AVOBENZONE 28.5 mg/1 mL; HOMOSALATE 140 mg/1 mL; OCTINOXATE 71.2 mg/1 mL; OCTISALATE 47.5 mg/1 mL; OCTOCRYLENE 95 mg/1 mL
INACTIVE INGREDIENTS: WATER; DIISOPROPYL ADIPATE; POLYOXYL 20 CETOSTEARYL ETHER; PROPANEDIOL; CAPRYLYL TRISILOXANE; ARACHIDYL ALCOHOL; PENTYLENE GLYCOL; DOCOSANOL; BETASIZOFIRAN; PROPYLENE GLYCOL; ARACHIDYL GLUCOSIDE; GLYCERYL CAPRYLATE; POTASSIUM CETYL PHOSPHATE; .ALPHA.-TOCOPHEROL ACETATE; HYDROXYETHYL ACRYLATE/SODIUM ACRYLOYLDIMETHYL TAURATE COPOLYMER (100000 MPA.S AT 1.5%); GLYCERIN; BETAINE; LIMONENE, (+)-; PECTIN; MELANIN SYNTHETIC (TYROSINE, PEROXIDE); SODIUM CHLORIDE; POLYSORBATE 60; SORBITAN ISOSTEARATE; SUCROSE; ISOMETHYL-.ALPHA.-IONONE; ETHYLHEXYLGLYCERIN; CAPRYLOYL GLYCINE; HAMAMELIS VIRGINIANA LEAF; HYALURONATE SODIUM; WHEAT; CAPRYLYL GLYCOL; XANTHAN GUM

Sun Logic Creme Solaire Visage et corps SPF 30

Active ingredients

Avobenzone 2.85%

Homosalate 14.00%

Octinoxate 7.12%

Octisalate 4.75%

Octocrylene 9.50%

purpose

Sunscreen

Uses

- Helps prevent sunburn
- If used as directed with other sun protection measures (see Directions), decreases the risk of skin cancer and early skin aging caused by the sun

Warnings

- For external use only

Do not use

on damaged or broken skin

When using this product

keep out of eyes. Rinse with water to remove

Stop use and ask

a doctor if rash occurs

Keep out of reach of children.

If product is swallowed, get medical help or contact a Poison Control Center right away.

Directions

- Apply liberally 15 minutes before sun exposure
- Reapply at least every 2 hours
- Use a water resistant sunscreen if swimming or sweating
- Sun Protection Measures: Spending time in the sun increases your risk of skin cancer and early skin aging. To decrease this risk, regularly use a sunscreen with a broad spectrum SPF of 15 or higher and other sun protection measures including:

- Limit time in the sun, especially from 10 a.m. to 2 p.m.

- Wear long-sleeve shirts, pants, hats, and sunglasses

- Children under 6 months: Ask a doctor.

Other information

- Protect this product from excessive heat and direct sun
- Store below 30°C/86°F

Inactive ingredients

Water/Eau (Aqua), Diisopropyl Adipate, Ceteareth-20, Propanediol, Caprylyl Methicone, Arachidyl Alcohol, Pentylene Glycol, Behenyl Alcohol, Sclerotium Gum, Fragrance (Parfum), Propylene Glycol, Arachidyl Glucoside, Glyceryl Caprylate, Potassium Cetyl Phosphate, Tocopheryl Acetate, C30-45 Alkyl Cetearyl Dimethicone Crosspolymer, Hydroxyethyl Acrylate/Sodium Acryloyldimethyl Taurate Copolymer, Glycerin, Betaine, Limonene, Pectin, Melanin, Sodium Chloride, Polysorbate 60, Sorbitan Isostearate, DNA, Sucrose, Alpha-Isomethyl Ionone, Glyceryl Acrylate/Acrylic Acid Copolymer, Ethylhexylglycerin, Capryloyl Glycine, Hamamelis Virginiana (Witch Hazel) Leaf Extract, Sodium Hyaluronate, Triticum Vulgare (Wheat) Germ Protein, Caprylyl Glycol, Xanthan Gum. 01